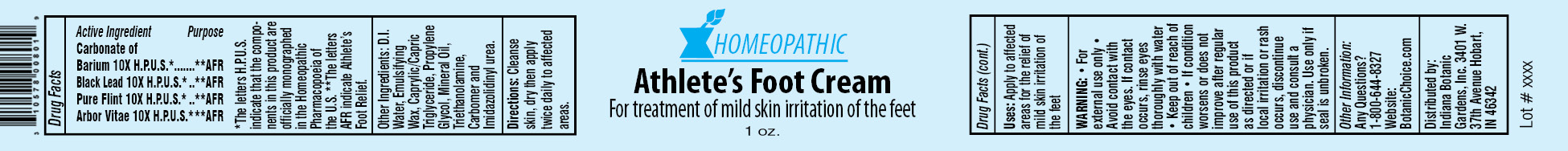 DRUG LABEL: Homeopathic Athletes Foot
NDC: 10578-008 | Form: CREAM
Manufacturer: Indiana Botanic Gardens
Category: homeopathic | Type: HUMAN OTC DRUG LABEL
Date: 20120427

ACTIVE INGREDIENTS: BARIUM CARBONATE 10 [hp_X]/28 g; GRAPHITE 10 [hp_X]/28 g; SILICON DIOXIDE 10 [hp_X]/28 g; THUJA OCCIDENTALIS LEAFY TWIG 10 [hp_X]/28 g
INACTIVE INGREDIENTS: WATER; CETOSTEARYL ALCOHOL; POLYSORBATE 60; TRICAPRYLIN; PROPYLENE GLYCOL; MINERAL OIL; TROLAMINE; CARBOMER 934; IMIDUREA

Homeopathic Athletes Foot Cream

Active Ingredients

Carbonate of Barium 10X H.P.U.S.*

Black Lead 10X H.P.U.S.*

Pure Flint 10X H.P.U.S.*

Arbor Vitae 10X H.P.U.S.*

Purpose

**AFR

**AFR

**AFR

**AFR

*The letters H.P.U.S. indicate that the components in this product are officially monographed in the Homeopathic Pharmacopoeia of the U.S. **The letters AFR indicate Athlete’s Foot Relief.

Other Ingredients:

D.I. Water, Emulsifying Wax, Caprylic/Capric Triglyceride, Propylene Glycol, Mineral Oil, Triethanolamine, Carbomer and Imidazolidinyl urea.

Directions:

Cleanse skin, dry then apply twice daily to affected areas.

Uses:

Apply to affected areas for the relief of mild skin irritation of the feet

WARNING:

- for external use only
- Avoid contact with the eyes. If contact occurs, rinse eyes thoroughly with water

- Keep out of reach of children

STOP USE

- If condition worsens or does not improve after regular use of this product as directed or if local irritation or rash occurs, discontinue use and consult a physician.

Use only if seal is unbroken.

Other Information:

Any Questions?

1-800-644-8327

Website:

BotanicChoice.com

Distributed by:

Indiana Botanic Gardens, Inc. 3401 W. 37th Avenue Hobart, IN 46342

Homeopathic Athlete’s Foot Cream

For treatment of mild skin irritation of the feet

1 oz.